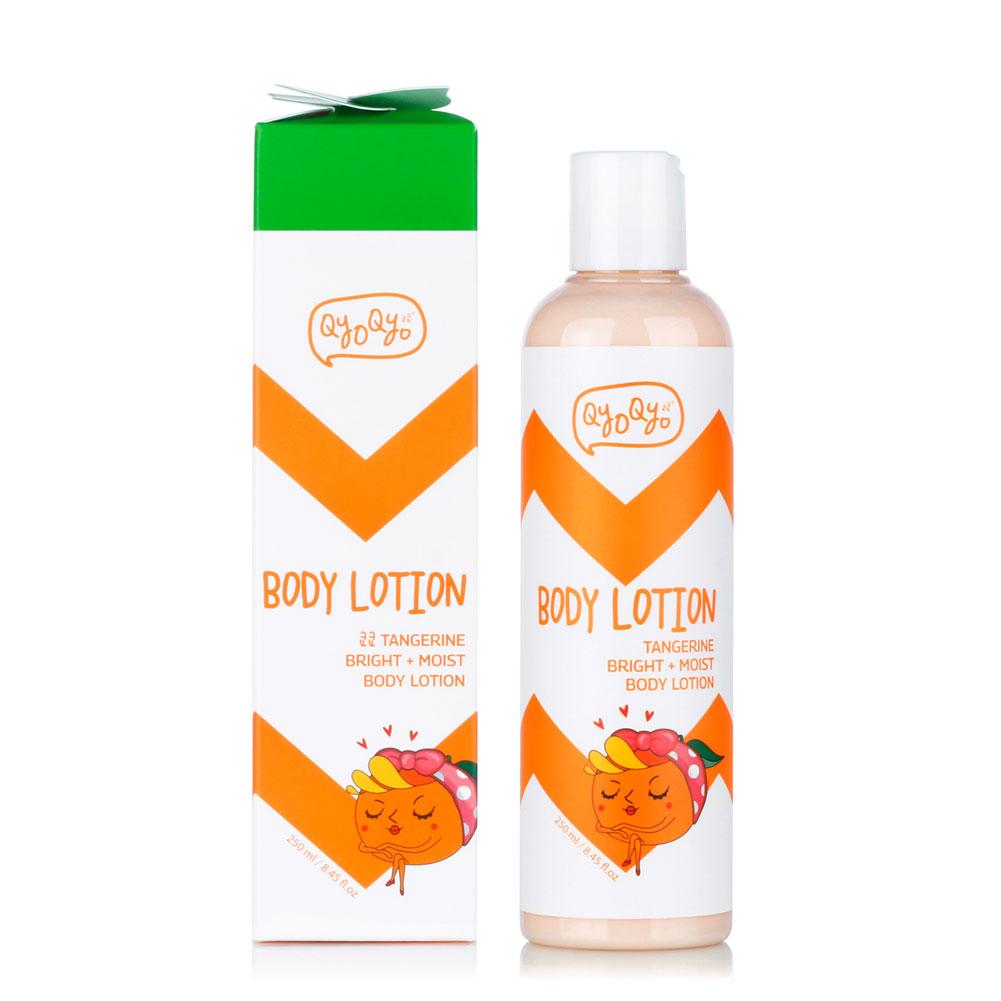 DRUG LABEL: QYO QYO Tangerine Bright Moist Body
NDC: 71733-107 | Form: LOTION
Manufacturer: LaLa Co., Ltd.
Category: otc | Type: HUMAN OTC DRUG LABEL
Date: 20190101

ACTIVE INGREDIENTS: DIMETHICONE 0.2 g/250 mL; GLYCERIN 9.5 g/250 mL
INACTIVE INGREDIENTS: CETYL ETHYLHEXANOATE; BUTYLENE GLYCOL; MINERAL OIL; TANGERINE PEEL; WATER; PETROLATUM

Qyo Qyo Tangerine Bright + Moist
Body Lotion

ACTIVE INGREDIENTS

DIMETHICONE 0.2%

GLYCERIN 9.5%

PURPOSE

SKIN PROTECTANT

USES

- Helps prevent and temporarily protects chapped or cracked skin.

WARNINGS

For external use only.

When using this product • do not get into eyes.

STOP USE

Stop us and ask doctor if • condition worsens • symptoms last
more than 7 days or clear up and occurs again within a few days.

Keep out of reach of children. If product is swallowed, get medical help or contact a Poison Control Center right away.

Directions

• Apply as needed. • After cleansing your body, apply a proper amount on skin and spread lightly for absorption.

Inactive Ingredients

Water, Butylene Glycol, Mineral Oil, Petrolatum, Cetyl Ethylhexanoate, Macadamia Ternifolia Seed Oil, Stearic Acid, Cetyl Alcohol

Other Information

Protect this product from excessive heat and direct sun.

Questions or Comments?

Call toll free 1-800-311-6680